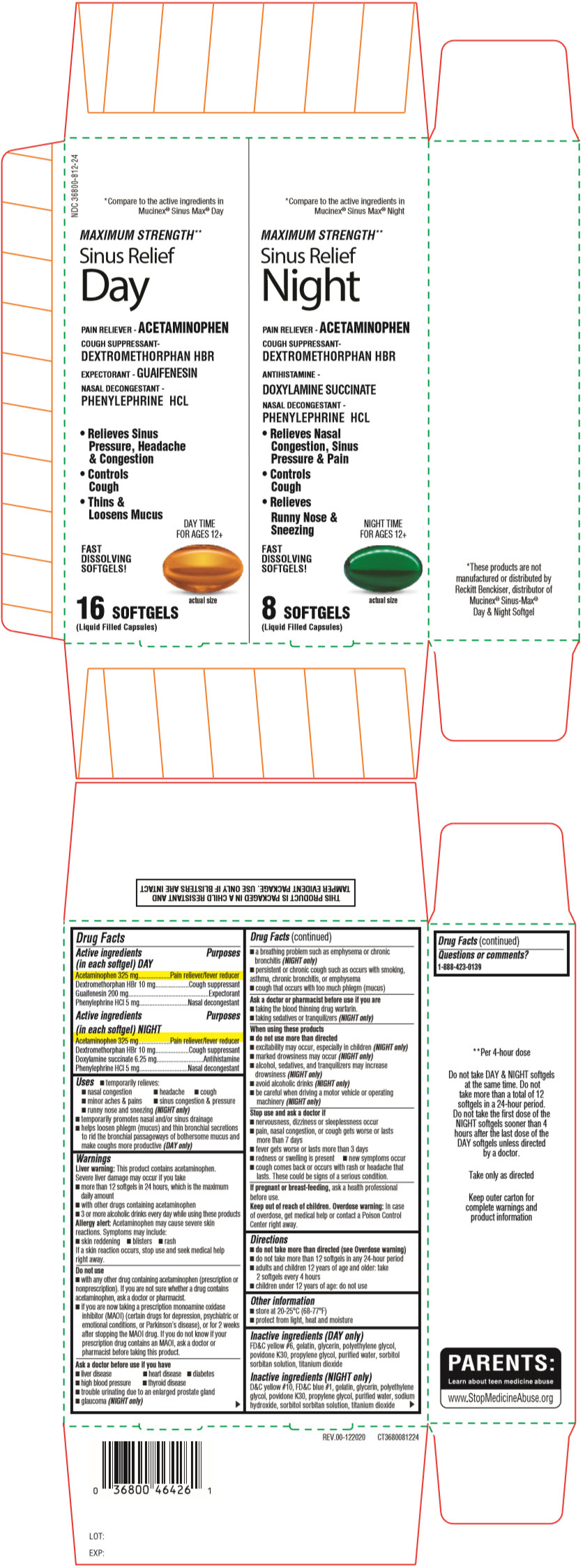 DRUG LABEL: Sinus Max Relief Day and Night
NDC: 36800-765 | Form: KIT | Route: ORAL
Manufacturer: TOPCO ASSOCIATES LLC
Category: otc | Type: HUMAN OTC DRUG LABEL
Date: 20210315

ACTIVE INGREDIENTS: ACETAMINOPHEN 325 mg/1 1; DEXTROMETHORPHAN HYDROBROMIDE 10 mg/1 1; GUAIFENESIN 200 mg/1 1; PHENYLEPHRINE HYDROCHLORIDE 5 mg/1 1; ACETAMINOPHEN 325 mg/1 1; DEXTROMETHORPHAN HYDROBROMIDE 10 mg/1 1; DOXYLAMINE SUCCINATE 6.25 mg/1 1; PHENYLEPHRINE HYDROCHLORIDE 5 mg/1 1
INACTIVE INGREDIENTS: FD&C YELLOW NO. 6; GELATIN, UNSPECIFIED; GLYCERIN; POLYETHYLENE GLYCOL, UNSPECIFIED; POVIDONE, UNSPECIFIED; PROPYLENE GLYCOL; WATER; TITANIUM DIOXIDE; D&C YELLOW NO. 10; FD&C BLUE NO. 1; GELATIN, UNSPECIFIED; GLYCERIN; POLYETHYLENE GLYCOL, UNSPECIFIED; POVIDONE, UNSPECIFIED; PROPYLENE GLYCOL; WATER; SODIUM HYDROXIDE; TITANIUM DIOXIDE

Sinus Max Relief Day and Night

Drug Facts

ACTIVE INGREDIENT

PURPOSE

Active ingredients (in each softgel) DAY | Purposes
Acetaminophen 325 mg | Pain reliever/fever reducer
Dextromethorphan HBr 10 mg | Cough suppressant
Guaifenesin 200 mg | Expectorant
Phenylephrine HCl 5 mg | Nasal decongestant

Active ingredients (in each softgel) NIGHT | Purposes
Acetaminophen 325 mg | Pain reliever/fever reducer
Dextromethorphan HBr 10 mg | Cough suppressant
Doxylamine succinate 6.25 mg | Antihistamine
Phenylephrine HCl 5 mg | Nasal decongestant

Uses

- temporarily relieves:
  - nasal congestion
  - headache
  - cough
  - minor aches & pains
  - sinus congestion & pressure
  - runny nose and sneezing (NIGHT only)
- temporarily promotes nasal and/or sinus drainage
- helps loosen phlegm (mucus) and thin bronchial secretions to rid the bronchial passageways of bothersome mucus and make coughs more productive (DAY only)

Warnings

Liver warning

This product contains acetaminophen. Severe liver damage may occur if you take

- more than 12 softgels in 24 hours, which is the maximum daily amount
- with other drugs containing acetaminophen
- 3 or more alcoholic drinks every day while using these products

Allergy alert

Acetaminophen may cause severe skin reactions. Symptoms may include:

- skin reddening
- blisters
- rash

If a skin reaction occurs, stop use and seek medical help right away.

Do not use

- with any other drug containing acetaminophen (prescription or nonprescription). If you are not sure whether a drug contains acetaminophen, ask a doctor or pharmacist.
- if you are now taking a prescription monoamine oxidase inhibitor (MAOI) (certain drugs for depression, psychiatric or emotional conditions, or Parkinson's disease), or for 2 weeks after stopping the MAOI drug. If you do not know if your prescription drug contains an MAOI, ask a doctor or pharmacist before taking this product.

Ask a doctor before use if you have

- liver disease
- heart disease
- diabetes
- high blood pressure
- thyroid disease
- trouble urinating due to an enlarged prostate gland
- glaucoma (NIGHT only)
- a breathing problem such as emphysema or chronic bronchitis (NIGHT only)
- persistent or chronic cough such as occurs with smoking, asthma, chronic bronchitis, or emphysema
- cough that occurs with too much phlegm (mucus)

Ask a doctor or pharmacist before use if you are

- taking the blood thinning drug warfarin.
- taking sedatives or tranquilizers (NIGHT only)

When using these products

- do not use more than directed
- excitability may occur, especially in children (NIGHT only)
- marked drowsiness may occur (NIGHT only)
- alcohol, sedatives, and tranquilizers may increase drowsiness (NIGHT only)
- avoid alcoholic drinks (NIGHT only)
- be careful when driving a motor vehicle or operating machinery (NIGHT only)

Stop use and ask a doctor if

- nervousness, dizziness or sleeplessness occur
- pain, nasal congestion, or cough gets worse or lasts more than 7 days
- fever gets worse or lasts more than 3 days
- redness or swelling is present
- new symptoms occur
- cough comes back or occurs with rash or headache that lasts. These could be signs of a serious condition.

PREGNANCY OR BREAST FEEDING

If pregnant or breast-feeding, ask a health professional before use.

Keep out of reach of children.

Overdose warning

In case of overdose, get medical help or contact a Poison Control Center right away.

Directions

- do not take more than directed (see Overdose warning)
- do not take more than 12 softgels in any 24-hour period
- adults and children 12 years of age and older: take 2 softgels every 4 hours
- children under 12 years of age: do not use

Other information

- store at 20-25°C (68-77°F)
- protect from light, heat and moisture

Inactive ingredients (DAY only)

FD&C yellow #6, gelatin, glycerin, polyethylene glycol, povidone K30, propylene glycol, purified water, sorbitol sorbitan solution, titanium dioxide

Inactive ingredients (NIGHT only)

D&C yellow #10, FD&C blue #1, gelatin, glycerin, polyethylene glycol, povidone K30, propylene glycol, purified water, sodium hydroxide, sorbitol sorbitan solution, titanium dioxide

Questions or comments?

1-888-423-0139

PRINCIPAL DISPLAY PANEL - Kit Carton

NDC 36800-812-24

*Compare to the active ingredients in
Mucinex® Sinus Max® Day

MAXIMUM STRENGTH**

Sinus Relief
Day

PAIN RELIEVER - ACETAMINOPHEN
COUGH SUPPRESSANT-
DEXTROMETHORPHAN HBR
EXPECTORANT - GUAIFENESIN
NASAL DECONGESTANT -
PHENYLEPHRINE HCL

- Relieves Sinus
  Pressure, Headache
  & Congestion
- Controls
  Cough
- Thins &
  Loosens Mucus

DAY TIME
FOR AGES 12+

FAST
DISSOLVING
SOFTGELS!

actual size

16 SOFTGELS
(Liquid Filled Capsules)

*Compare to the active ingredients in
Mucinex® Sinus Max® Night

MAXIMUM STRENGTH**

Sinus Relief
Night

PAIN RELIEVER - ACETAMINOPHEN
COUGH SUPPRESSANT-
DEXTROMETHORPHAN HBR
ANTIHISTAMINE -
DOXYLAMINE SUCCINATE
NASAL DECONGESTANT -
PHENYLEPHRINE HCL

- Relieves Nasal
  Congestion, Sinus
  Pressure & Pain
- Controls
  Cough
- Relieves
  Runny Nose &
  Sneezing

NIGHT TIME
FOR AGES 12+

FAST
DISSOLVING
SOFTGELS!

actual size

8 SOFTGELS
(Liquid Filled Capsules)